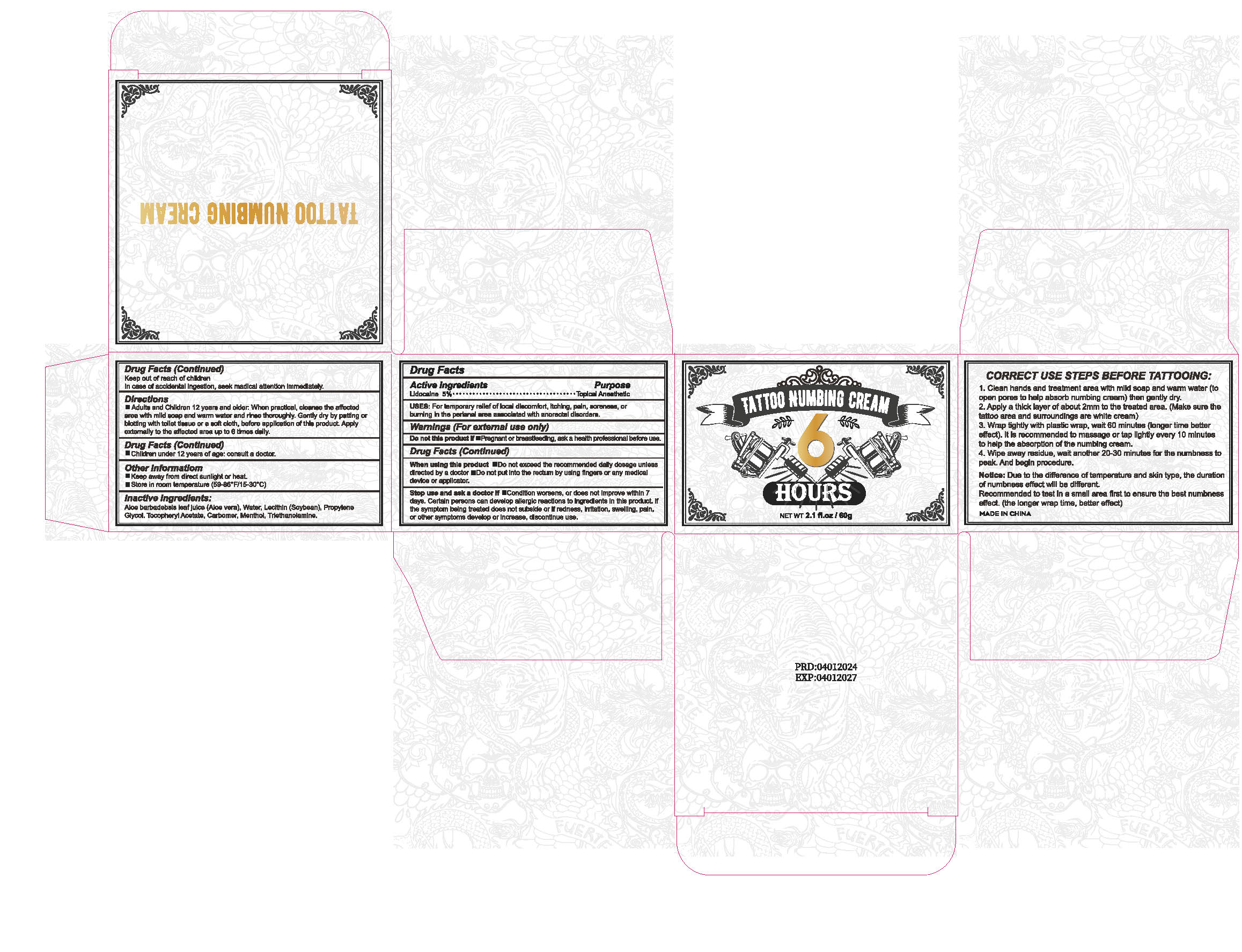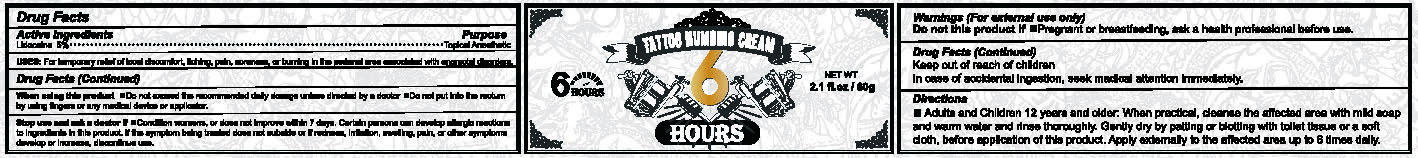 DRUG LABEL: Tattoo Numbing Cream
NDC: 84023-201 | Form: PASTE
Manufacturer: Shenzhen Yangan Technology Co., Ltd.
Category: otc | Type: HUMAN OTC DRUG LABEL
Date: 20240408

ACTIVE INGREDIENTS: LIDOCAINE 5 g/100 g
INACTIVE INGREDIENTS: ALOE; LECITHIN, SOYBEAN; PROPYLENE GLYCOL; CARBOMER HOMOPOLYMER, UNSPECIFIED TYPE; TROLAMINE; MENTHOL; WATER; ALPHA-TOCOPHEROL ACETATE

Tattoo Numbing Cream

Tattoo Numbing Cream

ACTIVE INGREDIENT

Lidocaine 5%

PURPOSE

Topical Anesthetic

INDICATIONS AND USAGE

For temporary relief of local discomfort, itching, pain, soreness, or burning in the perianal area associated with anorectal disorders.

WARNINGS

For external use only

DO NOT USE

Pregnant or breastfeeding, ask a health professional before use.

WHEN USING

Do not exceed the recommended daily dosage unless directed by a doctor.
Do not put into the rectum by using fingers or any medical device or applicator.

STOP USE

Condition worsens, or does not improve within 7 days. Certain persons can develop allergic reactions to ingredients in this product. If the symptom being treated does not subside or if redness, irritation,swelling, pain, or other symptoms develop or increase, discontinue use.

KEEP OUT OF REACH OF CHILDREN

In case of accidental ingestion, seek madical attention immediately.

DOSAGE AND ADMINISTRATION

Adults and Children 12 years and older: When practical, cleanse the affected area with mild soap and warm water and rinse thoroughly. Gently dry by patting or blotting with toilet tissue or a soft cloth, before application of this product. Apply externally to the affected area up to 6 times daily.

STORAGE AND HANDLING

Keep away from direct sunlight or heat.
Store in room temperature (59-86°F/15-30°C).

INACTIVE INGREDIENT

Aloe barbadebsis leaf juice (Aloe vera)
Water
Lecithin (Soybean)
Propylene Glycol
Tocopheryl Acetate
Carbomer
Menthol
Triethanolamine